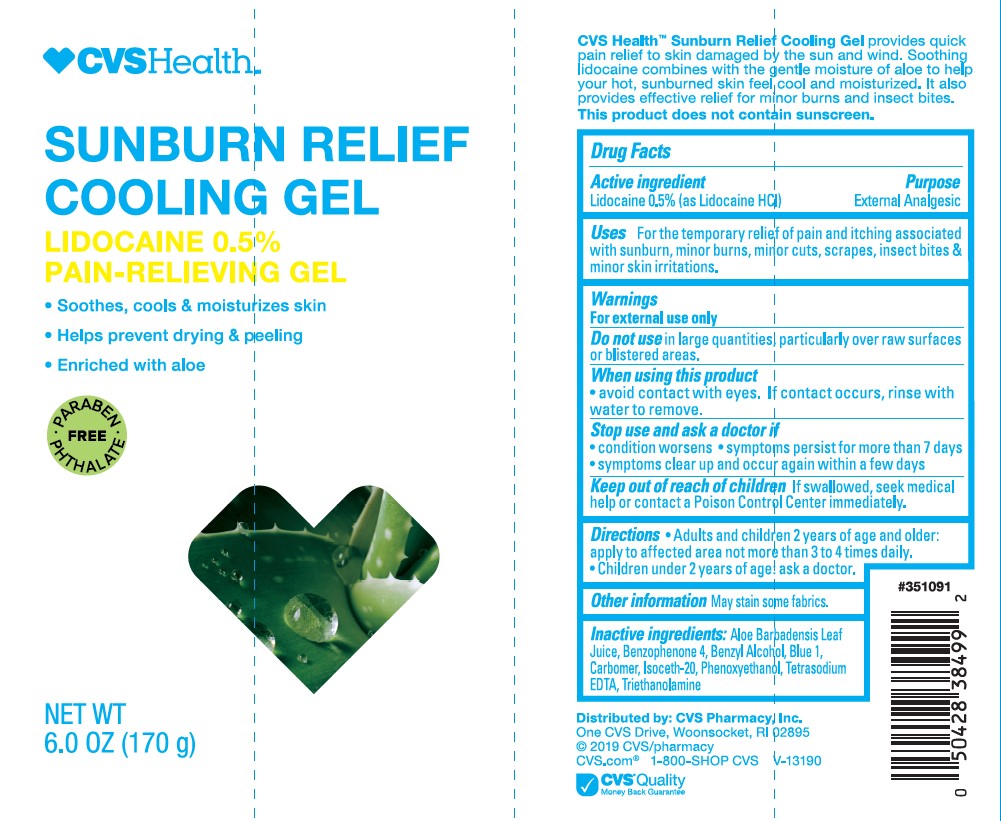 DRUG LABEL: CVS Health Sunburn Relief Cooling Lidocaine 0.5 Pain-Relieving
NDC: 51316-022 | Form: GEL
Manufacturer: CVS Pharmacy
Category: otc | Type: HUMAN OTC DRUG LABEL
Date: 20241017

ACTIVE INGREDIENTS: LIDOCAINE HYDROCHLORIDE 5 mg/1 g
INACTIVE INGREDIENTS: BENZYL ALCOHOL; SULISOBENZONE; PHENOXYETHANOL; FD&C BLUE NO. 1; EDETATE SODIUM; CARBOMER INTERPOLYMER TYPE A (ALLYL SUCROSE CROSSLINKED); TROLAMINE; ISOCETETH-20; ALOE VERA LEAF; WATER

CVS Health Sunburn Relief Cooling Gel Lidocaine 0.5% Pain-Relieving Gel

Active ingredients

Lidocaine 0.5% (as Lidocaine HCl)

Purpose

External Analgesic

Uses

For the temporary relief of pain and itching associated with sunburn, minor burns, minor cuts, scrapes, insect bites & minor skin irritations.

Warnings

For external use only

Do not use

in large quantities, particularly over raw surfaces or blistered areas.

When using this product

- avoid contact with eyes.. If contact occurs, rinse with water to remove.

Stop use and ask a doctor if

- condition worsens
- symptoms persist for more than 7 days
- symptomes clear up and occur again within a few days.

Keep out of reach of children.

- If swallowed, seek medical help or contact a Poison Control Center immediately.

Directions

- Adults and children 2 years and older: apply to affected area not more than 3 to 4 times daily.
- Children under 2 years of age: ask a doctor.

Other information

May stain some fabrics.

Inactive ingredients

Aloe Barbadensis Leaf Juice, Benzophenone-4, Benzyl Alcohol, Blue 1, Carbomer, Isoceteth-20, Phenoxyethanol, Tetrasodium EDTA, Triethanolamine.